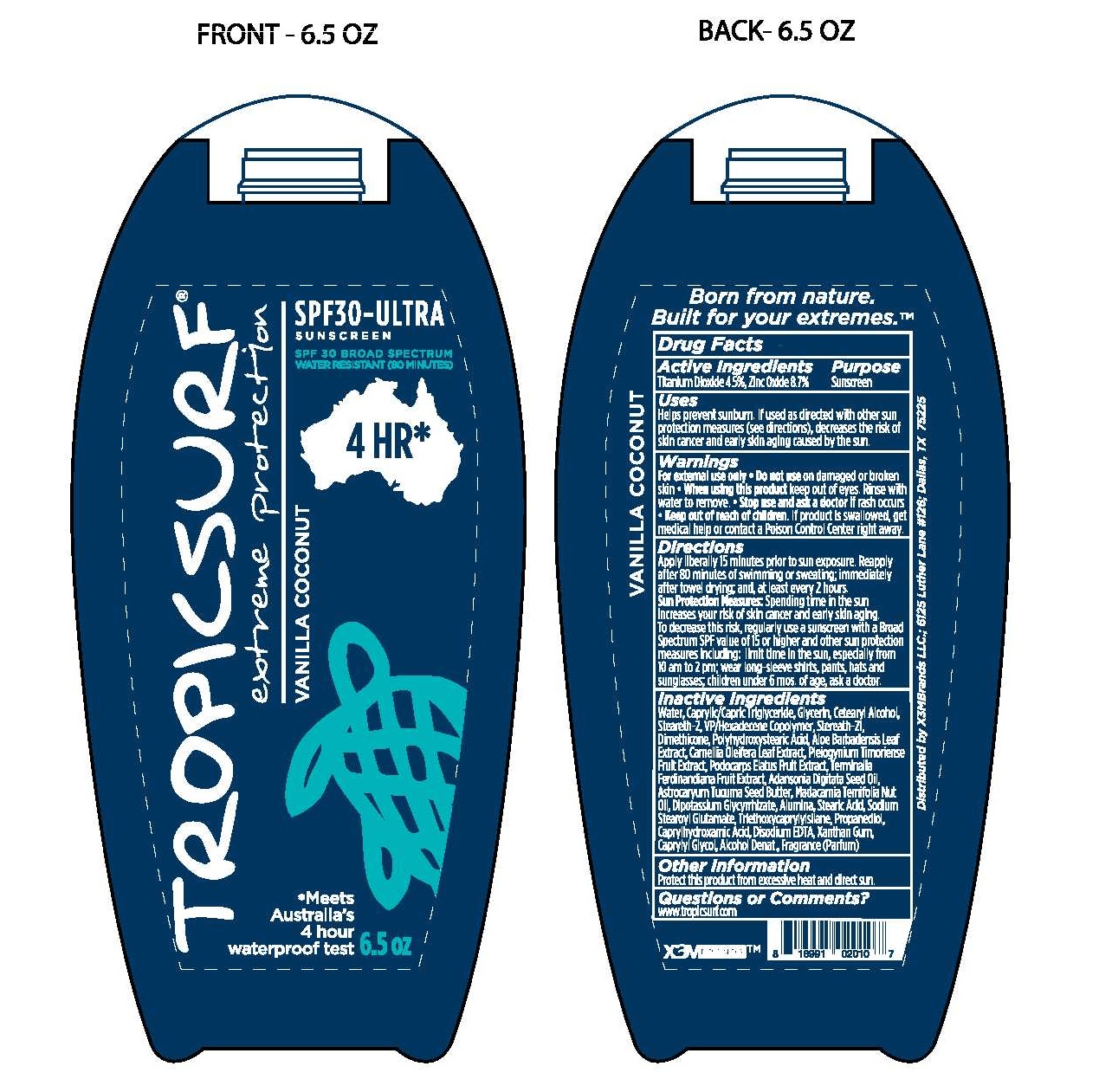 DRUG LABEL: TROPICSURF EXTREME PROTECTION SPF30-ULTRA
NDC: 70884-101 | Form: LOTION
Manufacturer: PALMER SURF LLC (DBA X3EMBRANDS)
Category: otc | Type: HUMAN OTC DRUG LABEL
Date: 20171107

ACTIVE INGREDIENTS: TITANIUM DIOXIDE 4.5 g/100 mL; ZINC OXIDE 8.7 g/100 mL
INACTIVE INGREDIENTS: WATER; MEDIUM-CHAIN TRIGLYCERIDES; GLYCERIN; CETOSTEARYL ALCOHOL; STEARETH-2; VINYLPYRROLIDONE/HEXADECENE COPOLYMER; STEARETH-21; DIMETHICONE; POLYHYDROXYSTEARIC ACID (2300 MW); ALOE VERA LEAF; CAMELLIA OLEIFERA LEAF; PLUM; PODOCARPUS ELATUS WHOLE; KAKADU PLUM; ADANSONIA DIGITATA SEED OIL; ASTROCARYUM ACULEATUM SEED OIL; MACADAMIA OIL; GLYCYRRHIZINATE DIPOTASSIUM; ALUMINUM OXIDE; STEARIC ACID; SODIUM STEAROYL GLUTAMATE; TRIETHOXYCAPRYLYLSILANE; PROPANEDIOL; CAPRYLHYDROXAMIC ACID; DISODIUM EDTA-COPPER; XANTHAN GUM; CAPRYLYL GLYCOL; ALCOHOL

ACTIVE INGREDIENTS

- TITANIUM DIOXIDE 4.5%
- ZINC OXIDE 8.7%

DIRECTIONS

- APPLY LIBERALLY 15 MINUTES PRIOR TO SUN EXPOSURE. REAPPLY AFTER
- 80 MINUTES OF SWIMMING OR SWEATING; IMMEDIATELY AFTER TOWEL
- DRYING; AND, AT LEAST EVERY 2 HOURS.

SUN PROTECTION MEASURES:

- SPENDING TIME IN THE SUN INCREASES YOUR RISKI OF SKIN CANCER AND EARLY SKIN
- AGING. TO DECREASE THIS RISK, REGULARLY USE A SUNSCREEN WITH A BROAD
- SPECTRUM SPF VALUE OF 15 OR HIGHER AND OTHER SUN PROTECTION MEASURES
- INCLUDING: LIMIT TIME IN THE SUN, ESPECIALLY FROM 10 AM TO 2 PM; WEAR
- LONG-SLEEVE SHIRTS, PANTS, HATS AND SUNGLASSES; CHILDREN UNDER 6 MOS.
- OF AGE, ASK A DOCTOR

PURPOSE

- SUNSCREEN

USES

- HELPS PREVENT SUNBURN
- IF USED AS DIRECTED WITH OTHER SUN PROTECTION MEASURES (SEE DIRECTIONS),
- DECREASES THE RISK OF SKIN CANCER AND EARLY SKIN AGING CAUSED BY THE SUN.

WARNINGS

FOR EXTERNAL USE ONLY

DO NOT USE ON DAMAGED OR BROKEN SKIN

WHEN USING THIS PRODUCT

- KEEP OUT OF THE EYES.
- RINSE WITH WATER TO REMOVE

STOP USE AND ASK A DOCTOR IF

- IF RASH OCCURS

KEEP OUT OF REACH OF CHILDREN.

- IF PRODUCT IS SWALLOWED, GET MEDICAL HELP OR CONTACT A POISON CONTROL CENTER RIGHT AWAY.

INACTIVE INGREDIENTS

WATER, CAPRYLIC/CAPRIC TRIGLYCERIDE, GLYCERIN, CETEARYL ALCOHOL, STEARETH-2, VP/HEXADECENE COPOLYMER,

STEREATH-21, DIMETHICONE, POLYHYDROXYSTEARIC ACID, ALOE BARBADENSIS LEAF EXTRACT, CAMELLIA OLEIFERA

LEAF EXTRACT, PLEIOGYNIUM TIMORIENSE FRUIT EXTRACT, PODOCARPS ELATUS FRUIT EXTRACT, TERMINALIA FERDINANDIANA

FRUIT EXTRACT, ADANSONIA DIGITATA SEED OIL, ASTROCARYUM TUCUMA SEED BUTTER, MADACAMIA TERNIFOLIA NUT OIL,

DIPOTASSIUM GLYCYRRHIZATE, ALUMINA, STEARIC ACID, SODIUM STEAROYL GLUTAMATE, TRIETHOXYCAPRYLYLSILANE,

PROPANEDIOL, CAPRYLHYDROXAMIC ACID, DISODIUM EDTA, XANTHAN GUM, CAPRYLYL GLYCOL, ALCOHOL DENAT.,

FRAGRANCE (PARFUM)